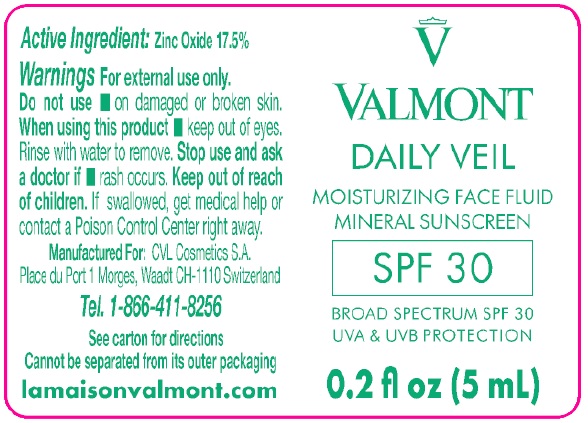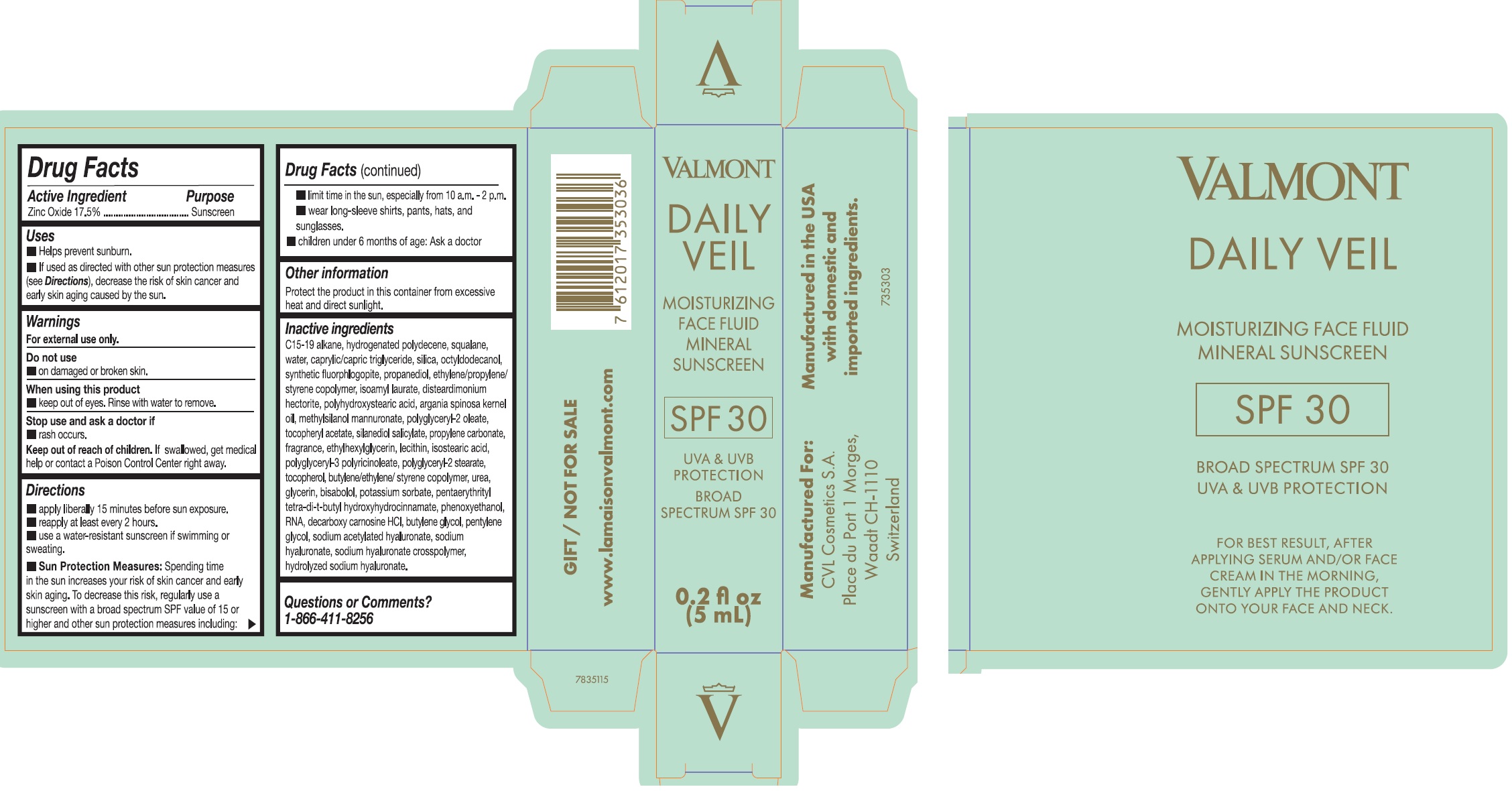 DRUG LABEL: Valmont Daily Veil Moisturizing Face Fluid Mineral Sunscreen SPF 30
NDC: 83883-001 | Form: GEL
Manufacturer: CVL Cosmetics North America Inc
Category: otc | Type: HUMAN OTC DRUG LABEL
Date: 20260116

ACTIVE INGREDIENTS: ZINC OXIDE 175 mg/1 mL
INACTIVE INGREDIENTS: C15-19 ALKANE; SQUALANE; WATER; MEDIUM-CHAIN TRIGLYCERIDES; SILICON DIOXIDE; OCTYLDODECANOL; MAGNESIUM POTASSIUM ALUMINOSILICATE FLUORIDE; PROPANEDIOL; ISOAMYL LAURATE; DISTEARDIMONIUM HECTORITE; ARGAN OIL; POLYGLYCERYL-2 OLEATE; .ALPHA.-TOCOPHEROL ACETATE; SILANEDIOL SALICYLATE; PROPYLENE CARBONATE; ETHYLHEXYLGLYCERIN; ISOSTEARIC ACID; POLYGLYCERYL-2 STEARATE; TOCOPHEROL; UREA; GLYCERIN; BISABOLOL; POTASSIUM SORBATE; PENTAERYTHRITOL TETRAKIS(3-(3,5-DI-TERT-BUTYL-4-HYDROXYPHENYL)PROPIONATE); PHENOXYETHANOL; DECARBOXY CARNOSINE HYDROCHLORIDE; BUTYLENE GLYCOL; PENTYLENE GLYCOL; SODIUM ACETYLATED HYALURONATE; SODIUM HYALURONATE

Valmont Daily Veil Moisturizing Face Fluid Mineral Sunscreen SPF 30

Active Ingredient

Zinc Oxide 17.5%

Purpose

Sunscreen

Uses

- Helps prevent sunburn
- If used as directed with other sun protection measures (see Directions), decreases the risk of skin cancer and early skin aging caused by the sun.

Warnings

For external use only.

Do not use

- on damaged or broken skin.

When using this product

- keep out of eyes. Rinse with water to remove.

Stop use and ask a doctor if

- rash occurs.

Keep out of reach of children.

If swallowed, get medical help or contact a Poison Control Center right away.

Directions

- apply liberally 15 minutes before sun exposure.
- reapply at least every 2 hours.
- use a water-resistant sunscreen if swimming or sweating.
- Sun Protection Measures:Spending time in the sun increases your risk of skin cancer and early skin aging. To decrease this risk, regularly use a sunscreen with a broad spectrum SPF value of 15 or higher and other sun protection measures including:
- limit time in the sun, especially from 10 a.m. - 2 p.m.
- wear long-sleeved shirt, pants, hats and sunglasses.
- children under 6 months of age: Ask a doctor.

Other information

Protect the product in this container from excessive heat or direct sunlight.

Inactive ingredients

C15-19 alkane, hydrogenated polydecene, squalane, water, caprylic/capric triglyceride, silica, octyldodecanol, synthetic fluorphlogopite, propanediol, ethylene/propylene/ styrene copolymer, isoamyl laurate, disteardimonium hectorite, polyhydroxystearic acid, argania spinosa kernel oil, methylsilanol mannuronate, polyglyceryl-2 oleate, tocopheryl acetate, silanediol salicylate, propylene carbonate, fragrance, ethylhexylglycerin, lecithin, isostearic acid, polyglyceryl-3 polyricinoleate, polyglyceryl-2 stearate, tocopherol, butylene/ethylene/styrene copolymer, urea, glycerin, bisabolol, potassium sorbate, pentaerythrityl tetra-di-t-butyl hydroxyhydrocinnamate, phenoxyethanol, RNA, decarboxy carnosine HCL, butylene glycol, pentylene glycol, sodium acetylated hyaluronate, sodium hyaluronate, sodium hyaluronate crosspolymer, hydrolyzed sodium hyaluronate

Questions or comments?

1-866-411-8256